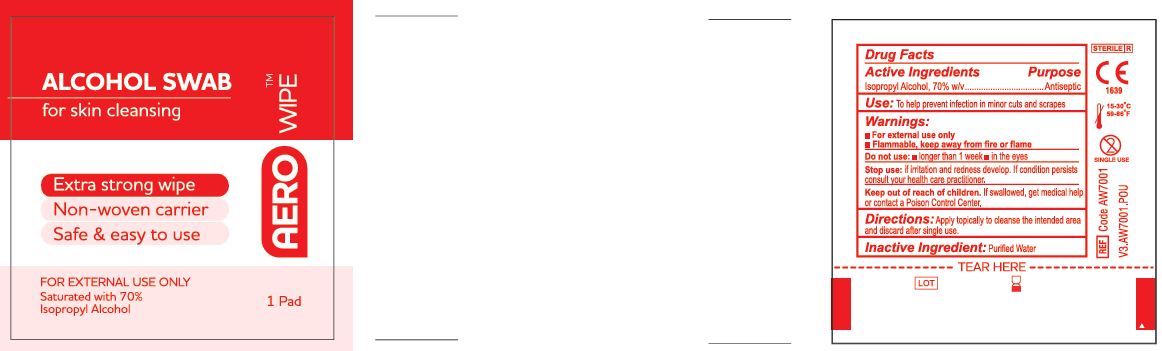 DRUG LABEL: Aerowipe
NDC: 55305-120 | Form: SWAB
Manufacturer: Aero Healthcare
Category: otc | Type: HUMAN OTC DRUG LABEL
Date: 20250710

ACTIVE INGREDIENTS: ISOPROPYL ALCOHOL 0.7 mL/1 mL
INACTIVE INGREDIENTS: WATER

AEROWIPE - Alcohol Swab

Use:

To help prevent infection in minor cuts and scrapes

Active Ingredient

Isopropyl Alcohol, 70% v/v

Warnings:

- For external use only
- Flammable, keep away from fire or flame

Do not use:

- Longer than 1 week
- In the eyes

Stop Use:

If irritation and redness develop. If condition persists consult your health care practitioner.

Keep out of reach of children.

If swallowed, get medical help or contact a Poison Control Center.

Directions

Apply topically to cleanse the intended area and discard after single use.

Inactive Ingredient

Purified Water

Purpose

Antiseptic

Package Label

AEROWIPE Alcohol Swab

LOT XXXXX

EXP XXXXXX